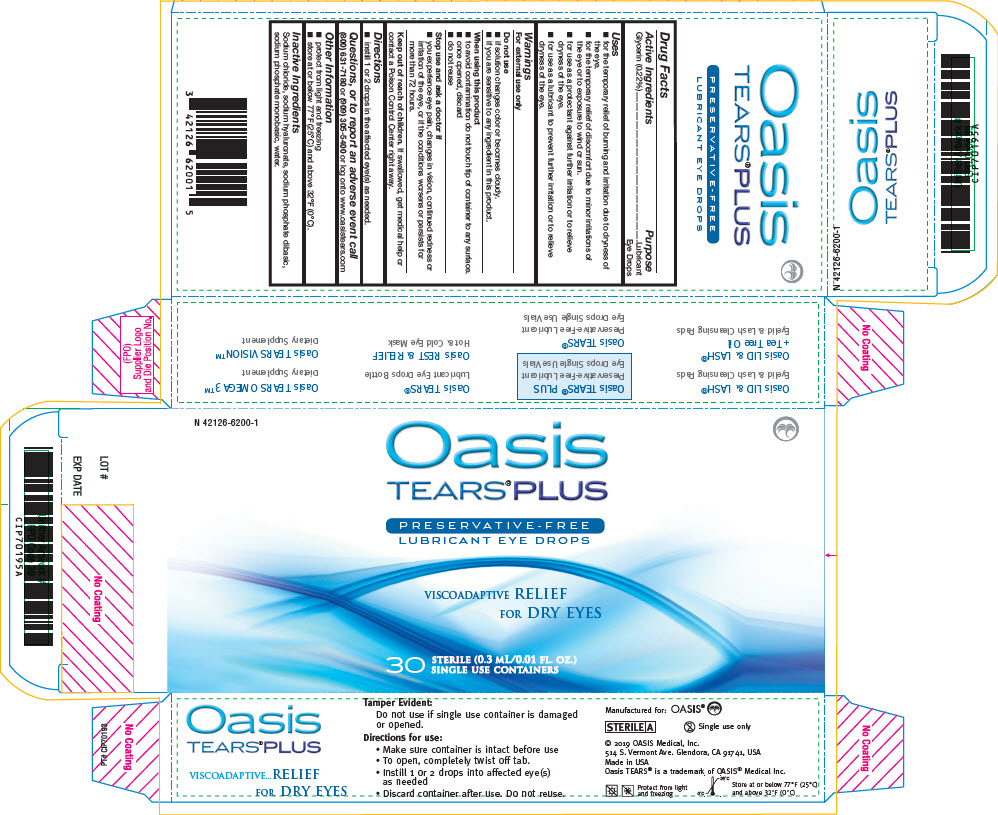 DRUG LABEL: OASIS Tears Plus
NDC: 42126-6200 | Form: SOLUTION/ DROPS
Manufacturer: OASIS Medical, Inc.
Category: otc | Type: HUMAN OTC DRUG LABEL
Date: 20250122

ACTIVE INGREDIENTS: GLYCERIN 0.22 g/100 mL
INACTIVE INGREDIENTS: HYALURONATE SODIUM 0.3 g/100 mL; SODIUM CHLORIDE; SODIUM PHOSPHATE, MONOBASIC, UNSPECIFIED FORM; SODIUM PHOSPHATE, DIBASIC, UNSPECIFIED FORM; WATER

Oasis Tears® Plus
Preservative-Free Lubricant Eye Drops

Drug Facts

Active Ingredients

Glycerin (0.22%)

Purpose

Lubricant Eye Drops

Uses

- for the temporary relief of burning and irritation due to dryness of the eye.
- for the temporary relief of discomfort due to minor irritations of the eye or to exposure to wind or sun.
- for use as a protectant against further irritation or to relieve dryness of the eye.
- for use as a lubricant to prevent further irritation or to relieve dryness of the eye.

Warnings

For external use only

Do not use

- if solution changes color or becomes cloudy.
- if you are sensitive to any ingredient in this product.

When using this product

- to avoid contamination do not touch tip of container to any surface.
- once opened, discard
- do not reuse

Stop use and ask a doctor if

- you experience eye pain, changes in vision, continued redness or irritation of the eye, or if the conditions worsens or persists for more than 72 hours.

Keep out of reach of children. If swallowed, get medical help or contact a Poison Control Center right away.

Directions

- instill 1 or 2 drops in the affected eye(s) as needed.

Questions, or to report an adverse event call

(800) 631-7180 or (909) 305-5400 or log onto www.oasistears.com

Other Information

- protect from light and freezing
- store at or below 77°F (25°C) and above 32°F (0°C).

Inactive Ingredients

Sodium chloride, sodium hyaluronate, sodium phosphate dibasic, sodium phosphate monobasic, water.

PRINCIPAL DISPLAY PANEL - 0.3 ML Vial Pouch Carton

N 42126-6200-1

Oasis
TEARS® PLUS

PRESERVATIVE-FREE
LUBRICANT EYE DROPS

VISCOADAPTIVE RELIEF
FOR DRY EYES

30
STERILE (0.3 ML/0.01 FL. OZ.)
SINGLE USE CONTAINERS